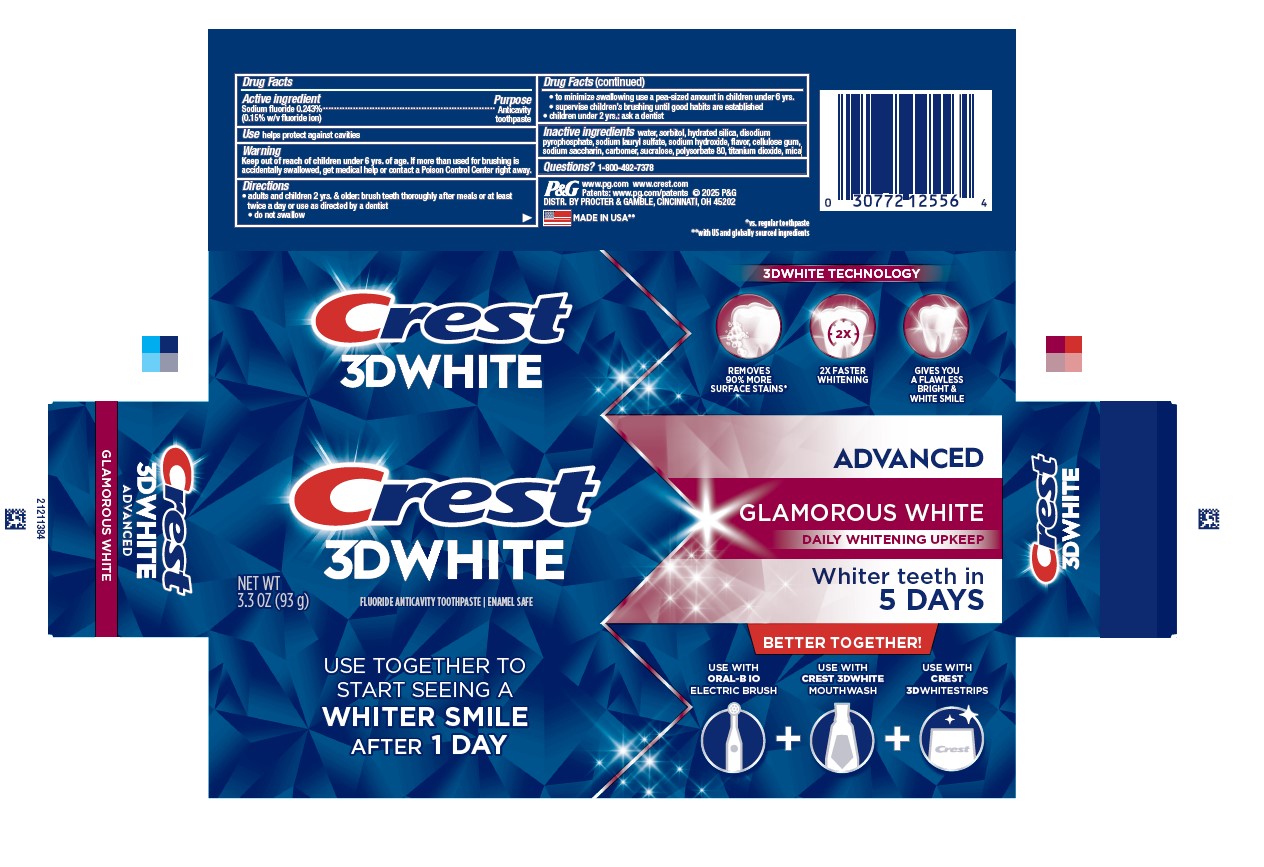 DRUG LABEL: Crest 3D White
NDC: 69423-768 | Form: PASTE, DENTIFRICE
Manufacturer: The Procter & Gamble Manufacturing Company
Category: otc | Type: HUMAN OTC DRUG LABEL
Date: 20250820

ACTIVE INGREDIENTS: SODIUM FLUORIDE 1.6 mg/1 g
INACTIVE INGREDIENTS: MICA; TITANIUM DIOXIDE; SODIUM SACCHARIN; CELLULOSE GUM; CARBOMER; SUCRALOSE; DISODIUM PYROPHOSPHATE; SORBITOL; HYDRATED SILICA; SODIUM LAURYL SULFATE; SODIUM HYDROXIDE; POLYSORBATE 80; WATER

Crest 3D White Advanced Glamorous White

Drug Facts

Active ingredient

Sodium fluoride 0.243% (0.16% w/v fluoride ion)

Purpose

Anticavity toothpaste

Use

helps protect against cavities

Warning

Keep out of reach of children under 6 yrs. of age. If more than used for brushing is accidentally swallowed, get medical help or contact a Poison Control Center right away.

Directions

- adults and children 2 yrs. & older: brush teeth thoroughly after meals or at least twice a day or use as directed by a dentist
- do not swallow
- to minimize swallowing use a pea-sized amount in children under 6
- supervise children's brushing until good habits are established
- children under 2 yrs.: ask a dentist

Inactive ingredients

water, sorbitol, hydrated silica, disodium
pyrophosphate, sodium lauryl sulfate, sodium hydroxide, flavor, cellulose gum,
sodium saccharin, carbomer, sucralose, polysorbate 80, titanium dioxide, mica

Questions?

1-800-492-7378

DISTR. BY PROCTER & GAMBLE, CINCINNATI, OH 45202

PRINCIPAL DISPLAY PANEL - 93 g Tube Carton

CREST

3D WHITE

ADVANCED

GLAMOROUS WHITE

DAILY WHITENING UPKEEP

WHITER TEETH IN 5 DAYS

NET WT 3.3 OZ (92 g)

FLUORIDE ANTICAVITY TOOTHPASTE

ENAMEL SAFE